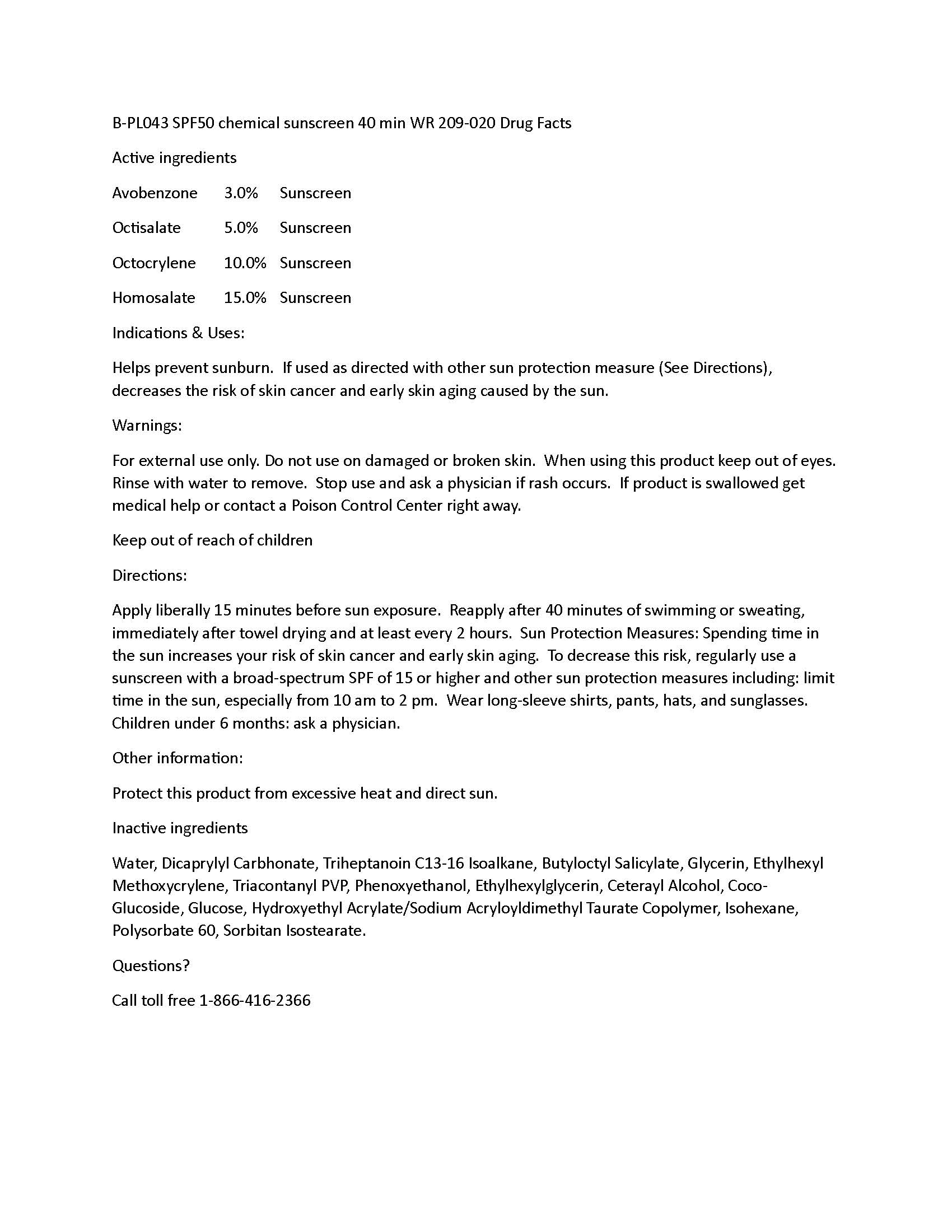 DRUG LABEL: Chemical Sunscreen SPF50
NDC: 60232-0043 | Form: SPRAY
Manufacturer: Swiss-American CDMO, LLC
Category: otc | Type: HUMAN OTC DRUG LABEL
Date: 20240508

ACTIVE INGREDIENTS: OCTISALATE 50 g/1000 g; AVOBENZONE 30 g/1000 g; HOMOSALATE 150 g/1000 g; OCTOCRYLENE 100 g/1000 g
INACTIVE INGREDIENTS: WATER; GLYCERIN; PHENOXYETHANOL; ETHYLHEXYLGLYCERIN; ARGAN OIL; TRIHEPTANOIN; COCO-GLUCOSIDE; DEXTROSE; CETOSTEARYL ALCOHOL; BUTYLOCTYL SALICYLATE; TRIACONTANYL PVP (WP-660); DICAPRYLYL CARBONATE; ETHYLHEXYL METHOXYCRYLENE; HYDROXYETHYL ACRYLATE/SODIUM ACRYLOYLDIMETHYL TAURATE COPOLYMER (100000 MPA.S AT 1.5%); ISOHEXADECANE; POLYSORBATE 60

Chemical Sunscreen SPF50

Warnings

For external use only. Do not use on damaged or broken skin. When using this product keep out of eyes. Rinse with water to remove. Stop use and ask a physician if rash occurs. If product is swallowed get medical help or contact a Poison Control Center right away.

Uses

Helps prevent sunburn. If used as directed with other sun protection measure (See Directions), decreases the risk of skin cancer and early skin aging caused by the sun.

Directions

Apply liberally 15 minutes before sun exposure. Reapply after 40 minutes of swimming or sweating, immediately after towel drying and at least every 2 hours. Sun Protection Measures: Spending time in the sun increases your risk of skin cancer and early skin aging. To decrease this risk, regularly use a sunscreen with a broad-spectrum SPF of 15 or higher and other sun protection measures including: limit time in the sun, especially from 10 am to 2 pm. Wear long-sleeve shirts, pants, hats, and sunglasses. Children under 6 months: ask a physician.

Active Ingredients

Avobenzone 3.0% Sunscreen
Octisalate 5.0% Sunscreen
Octocrylene 10.0% Sunscreen
Homosalate 15.0% Sunscreen

KEEP OUT OF REACH OF CHILDREN

Inactive Ingredients

Water, Dicaprylyl Carbhonate, Triheptanoin C13-16 Isoalkane, Butyloctyl Salicylate, Glycerin, Ethylhexyl Methoxycrylene, Triacontanyl PVP, Phenoxyethanol, Ethylhexylglycerin, Ceterayl Alcohol, Coco-
Glucoside, Glucose, Hydroxyethyl Acrylate/Sodium Acryloyldimethyl Taurate Copolymer, Isohexane, Polysorbate 60, Sorbitan Isostearate.

Purpose

Helps prevent sunburn. If used as directed with other sun protection measure (See Directions), decreases the risk of skin cancer and early skin aging caused by the sun.

Questions

Call toll free 1-866-416-2366